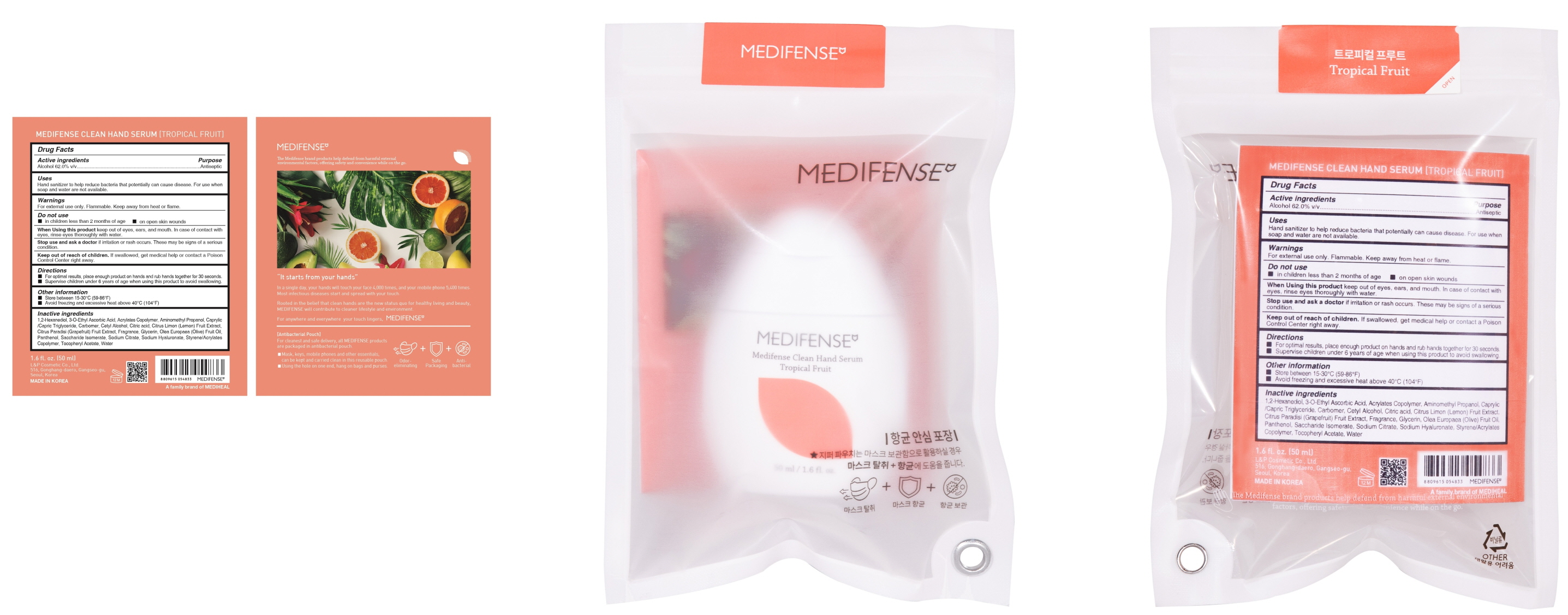 DRUG LABEL: MEDIFENSE CLEAN HAND SERUM TROPICAL FRUIT
NDC: 74005-070 | Form: LIQUID
Manufacturer: L&P Cosmetic Co., Ltd.
Category: otc | Type: HUMAN OTC DRUG LABEL
Date: 20201119

ACTIVE INGREDIENTS: ALCOHOL 31 mL/50 mL
INACTIVE INGREDIENTS: 1,2-Hexanediol; 3-O-Ethyl Ascorbic Acid; BUTYL ACRYLATE/METHYL METHACRYLATE/METHACRYLIC ACID COPOLYMER (18000 MW); AminomethylPropanol; MEDIUM-CHAIN TRIGLYCERIDES; CARBOMER HOMOPOLYMER, UNSPECIFIED TYPE; Cetyl Alcohol; CITRIC ACID MONOHYDRATE; Lemon; Grapefruit; Glycerin; OLIVE OIL; Panthenol; ROSEMARY; Saccharide Isomerate; Sage; SODIUM CITRATE, UNSPECIFIED FORM; HYALURONATE SODIUM; .ALPHA.-TOCOPHEROL ACETATE; Water

Active Ingredient(s)

ALCOHOL 62.0% v/v

Purpose

ANTISEPTIC

Warnings

For external use only. Flammable. Keep away from heat or flame
--------------------------------------------------------------------------------------------------------
Do not use
• in children less than 2 months of age
• on open skin wounds
--------------------------------------------------------------------------------------------------------
When using this product keep out of eyes, ears, and mouth. In case of contact with eyes, rinse eyes thoroughly with water.
--------------------------------------------------------------------------------------------------------
Stop use and ask a doctor if irritation or rash occurs. These may be signs of a serious condition.

Keep out of reach of children. If swallowed, get medical help or contact a Poison Control Center right away.

Uses

Hand sanitizer to help reduce bacteria that potentially can cause disease. For use when soap and water are not available.

Directions

• For optimal results, place enough product on hands and rub hands together for 30 seconds.
• Supervise children under 6 years of age when using this product to avoid swallowing.

Other information

• Store between 15-30C (59-86F)
• Avoid freezing and excessive heat above 40C (104F)

Inactive ingredients

1,2-Hexanediol, 3-O-Ethyl Ascorbic Acid, Acrylates Copolymer, Aminomethyl Propanol, Caprylic/Capric Triglyceride, Carbomer, Cetyl Alcohol, Citric acid, Citrus Limon (Lemon) Fruit Extract, Citrus Paradisi (Grapefruit) Fruit Extract, Fragrance, Glycerin, Olea Europaea (Olive) Fruit Oil, Panthenol, Saccharide Isomerate, Sodium Citrate, Sodium Hyaluronate, Styrene/Acrylates Copolymer, Tocopheryl Acetate, Water